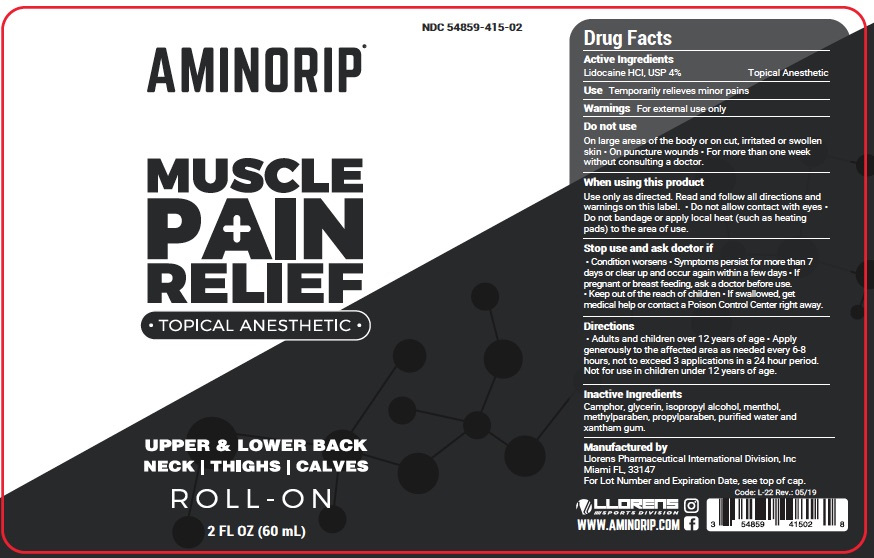 DRUG LABEL: Amino Rip Muscle Pain Relief
NDC: 54859-415 | Form: LIQUID
Manufacturer: LLORENS PHARMACEUTICALS INTERNATIONAL DIVISION
Category: otc | Type: HUMAN OTC DRUG LABEL
Date: 20260102

ACTIVE INGREDIENTS: LIDOCAINE 4 mg/100 mL
INACTIVE INGREDIENTS: ISOPROPYL ALCOHOL; MENTHOL; METHYLPARABEN; PROPYLPARABEN; WATER; XANTHAN GUM; CAMPHOR (SYNTHETIC); GLYCERIN

Amino Rip Muscle 415

Active Ingredients

Lidocaine HCl

Purpose

Topical Anesthetic

INDICATIONS AND USAGE

Use Temporarily relieves minor pains

Warnings For external use only

Do not use

- on large areas of the body or on cut, irritated or swollen skin
- on puncture wounds
- for more than one week without consulting a doctor.

When using this product

Use only as direct. Read and follow all directions and warnings on this label.

- Do not allow contact with eyes
- Do not bandage or apply local heat (such as heating pads) to the area of use.

Stop use and ask doctor if

- Condition worsens
- Symptoms persist for more than 7 days or clear up and occur again within a few days
- If pregnant or breast feeding, ask a doctor before use.
- Keep out of the reach of children
- If swallowed, get medical help or contact a Poison Control Center right away.

Keep out of reach of children.

Directions

- Adults and children over 12 years of age
- Apply generously to the affected area as needed every 6-8 hours, not to exceed 3 applications in a 24 hour period. Not for use in children under 12 years of age

Inactive ingredients

camphor, glycerin, isopropyl alcohol, menthol, methylparaben, propylparaben, purified water, xantham gum